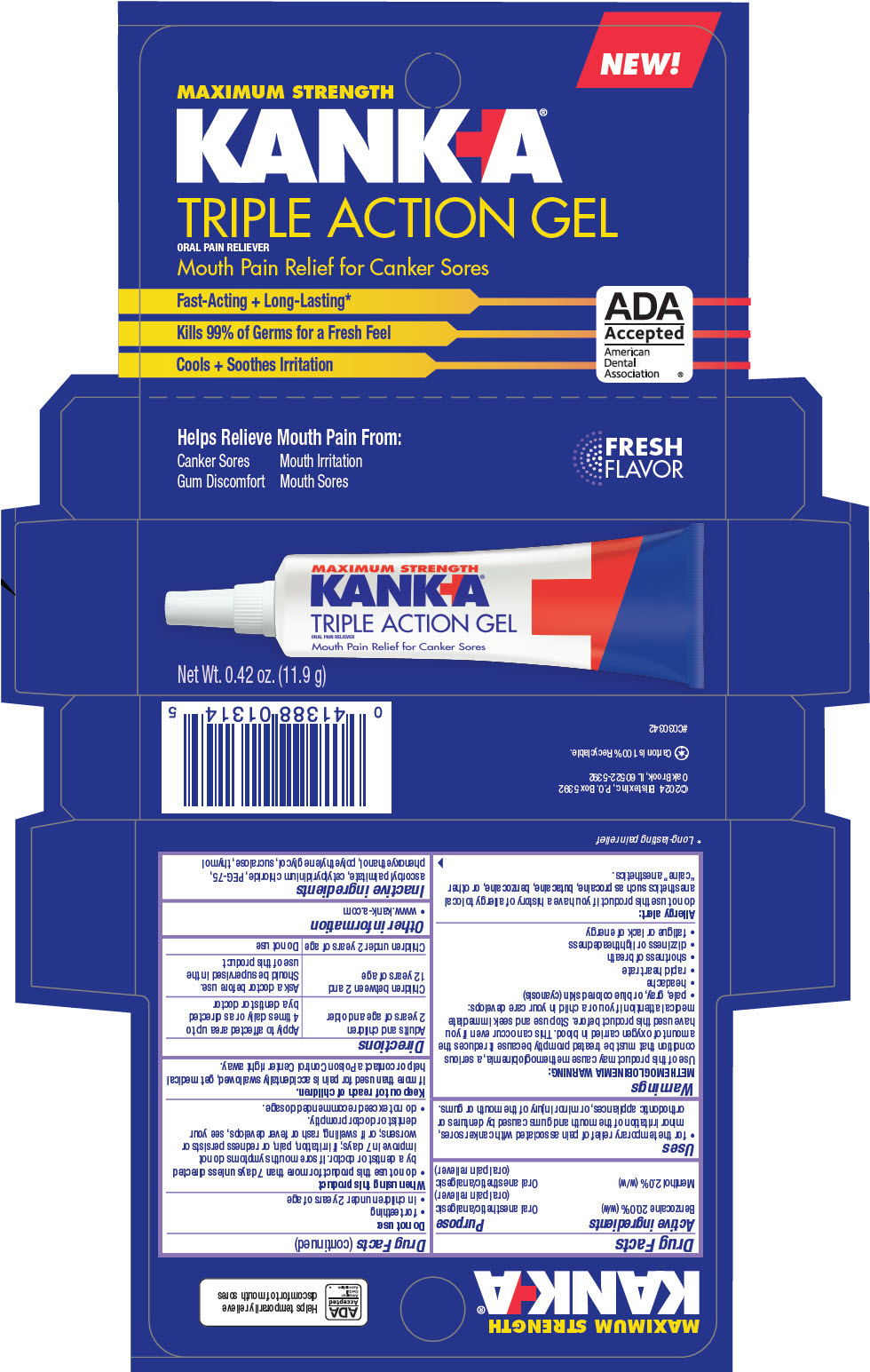 DRUG LABEL: Kanka Triple Action
NDC: 10157-2127 | Form: GEL
Manufacturer: Blistex Inc.
Category: otc | Type: HUMAN OTC DRUG LABEL
Date: 20250109

ACTIVE INGREDIENTS: BENZOCAINE 20 g/100 g; MENTHOL, UNSPECIFIED FORM 2 g/100 g
INACTIVE INGREDIENTS: POLYETHYLENE GLYCOL, UNSPECIFIED; POLYETHYLENE GLYCOL 3350; SUCRALOSE; PHENOXYETHANOL; ASCORBYL PALMITATE; THYMOL; CETYLPYRIDINIUM CHLORIDE

Kanka® Triple Action Gel

Drug Facts

ACTIVE INGREDIENT

Active ingredients | Purpose
Benzocaine 20.0% (w/w) | Oral anesthetic/analgesic (oral pain reliever)
Menthol 2.0% (w/w) | Oral anesthetic/analgesic (oral pain reliever)

Uses

- for the temporary relief of pain associated with canker sores, minor irritation of the mouth and gums caused by dentures or orthodontic appliances, or minor injury of the mouth or gums.

Warnings

METHEMOGLOBINEMIA WARNING

Use of this product may cause methemoglobinemia, a serious condition that must be treated promptly because it reduces the amount of oxygen carried in blood. This can occur even if you have used this product before. Stop use and seek immediate medical attention if you or a child in your care develops:

- pale, gray, or blue colored skin (cyanosis)
- headache
- rapid heart rate
- shortness of breath
- dizziness or lightheadedness
- fatigue or lack of energy

Allergy alert

do not use this product if you have a history of allergy to local anesthetics such as procaine, butacaine, benzocaine, or other "caine" anesthetics.

Do not use

- for teething
- in children under 2 years of age

When using this product

- do not use this product for more than 7 days unless directed by a dentist or doctor. If sore mouth symptoms do not improve in 7 days; if irritation, pain, or redness persists or worsens; or if swelling, rash or fever develops, see your dentist or doctor promptly.
- do not exceed recommended dosage.

Keep out of reach of children.

If more than used for pain is accidentally swallowed, get medical help or contact a Poison Control Center right away.

Directions

Adults and children 2 years of age and older | Apply to affected area up to 4 times daily or as directed by a dentist or doctor
Children between 2 and 12 years of age | Ask a doctor before use. Should be supervised in the use of this product
Children under 2 years of age | Do not use

Other information

- www.kank-a.com

Inactive ingredients

ascorbyl palmitate, cetylpyridinium chloride, PEG-75, phenoxyethanol, polyethylene glycol, sucralose, thymol

PRINCIPAL DISPLAY PANEL - 11.9 g Tube Carton

MAXIMUM STRENGTH

KANKA®

TRIPLE ACTION GEL
ORAL PAIN RELIEVER

Mouth Pain Relief for Canker Sores

Net Wt. 0.42 oz. (11.9 g)